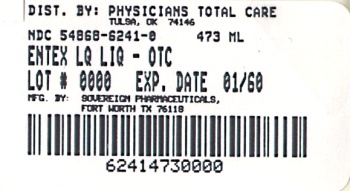 DRUG LABEL: ENTEX LQ
NDC: 54868-6241 | Form: LIQUID
Manufacturer: Physicians Total Care, Inc.
Category: otc | Type: HUMAN OTC DRUG LABEL
Date: 20100930

ACTIVE INGREDIENTS: GUAIFENESIN 100 mg/5 mL; PHENYLEPHRINE HYDROCHLORIDE 10 mg/5 mL
INACTIVE INGREDIENTS: BENZOIC ACID; ANHYDROUS CITRIC ACID; D&C RED NO. 33; EDETATE DISODIUM; GLYCERIN; PROPYLENE GLYCOL; WATER; SODIUM CITRATE; SORBITOL

Entex LQ

Drug Facts

Active Ingredients per teaspoon (5 mL)

Guaifenesin, USP 100 mg

Phenylephrine HCl, USP 10 mg

in each 5 mL (1 teaspoonful) red, strawberry flavored liquid

Purpose

Guaifenesin, USP Expectorant

Phenylephrine HCl, USP Nasal decongestant

Uses

- helps loosen phlegm (mucus) and thin bronchial secretions to drain bronchial tubes and make coughs more productive
- for the temporary relief of nasal and sinus congestion due to cold, hay fever or other respiratory allergies

WARNINGS

Do not exceed recommended dosage.

Do not use if you are now taking a prescription monoamine oxidase inhibitor (MAOI) (certain drugs for depression, psychiatric, or emotional conditions, or Parkinson’s Disease), or for two weeks after stopping the MAOI drug. If you do not know if your prescription drug contains an MAOI, ask a doctor or pharmacist before taking this drug.

Ask a doctor before use if you have

- a persistent or chronic cough such as occurs with smoking, asthma, chronic bronchitis or emphysema or where cough is accompanied by excessive phlegm (mucus).

Stop use and ask a doctor if

- nervousness, dizziness, or sleeplessness occur.
- symptoms do not improve within 7 days or are accompanied by fever.
- a cough persists for more than 1 week or is accompanied by a fever, rash or persistent headache.

Do not take this product if you have

- heart disease
- high blood pressure
- thyroid disease
- diabetes
- trouble urinating due to enlarged prostate gland
- breathing problems such as emphysema or chronic bronchitis.

If pregnant or breast-feeding,

- ask a health professional before use.

Keep out of reach of children

- In case of overdose, get medical help or contact a Poison Control Center immediately.

Directions

Age | Dose
Adults and children over 12 years of age | 1 teaspoonful (5mL) every 4 hours;
Children 6 to under 12 years of age | 1/2 teaspoonful (2.5 mL) every 4 hours;
Children 2 to under 6 years of age | 1/4 teaspoon (1.25mL) every 4 hours
Children under 2 years of age | Ask your doctor
Do not exceed 6 doses in a 24 – hour period.

Other information

- store at 20°- 25°C (68°- 77°F)

Inactive ingredients

benzoic acid USP, Bitter Masking agent, citric acid USP, D&C Red #33, edetate disodium, glycerin USP, propylene glycol USP, purified water, sodium citrate dihydrate USP, sorbitol solution and strawberry flavor.

Questions or Comments?

Call weekdays from 9 AM to 4PM CST at 1-888-252-3901 or go to http://www.wraser.com

email:medicalinfo@wraser.com

PACKAGE LABEL.PRINCIPAL DISPLAY PANEL

ENTEX LQ (guaifenesin and phenylephrine hydrochloride) liquid
473 mL (5 mL per teaspoon)
NDC 54868-6241-0